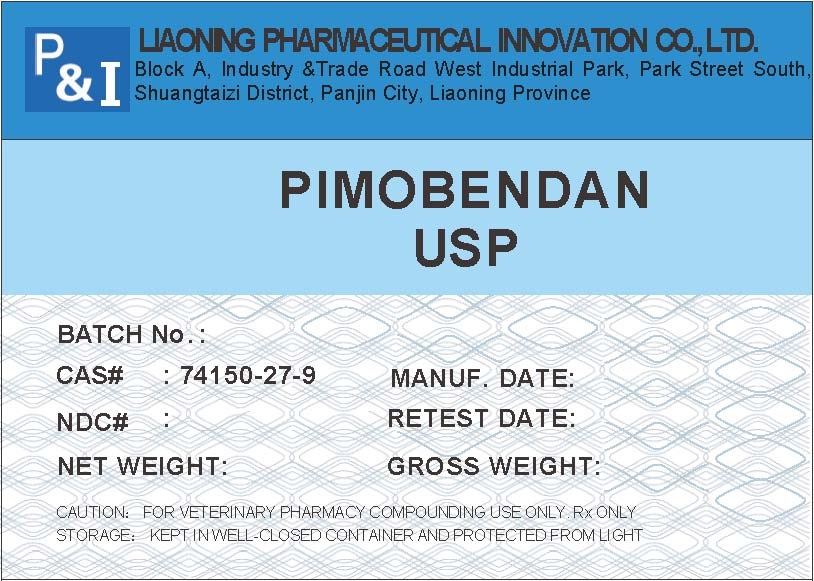 DRUG LABEL: pimobendan
NDC: 86212-002 | Form: POWDER
Manufacturer: Liaoning Pharmaceutical Innovation Co., Ltd.
Category: other | Type: BULK INGREDIENT - ANIMAL DRUG
Date: 20251117

ACTIVE INGREDIENTS: PIMOBENDAN 1 kg/1 kg

Pimobendan

Pimobendan_label_20241115.jpg